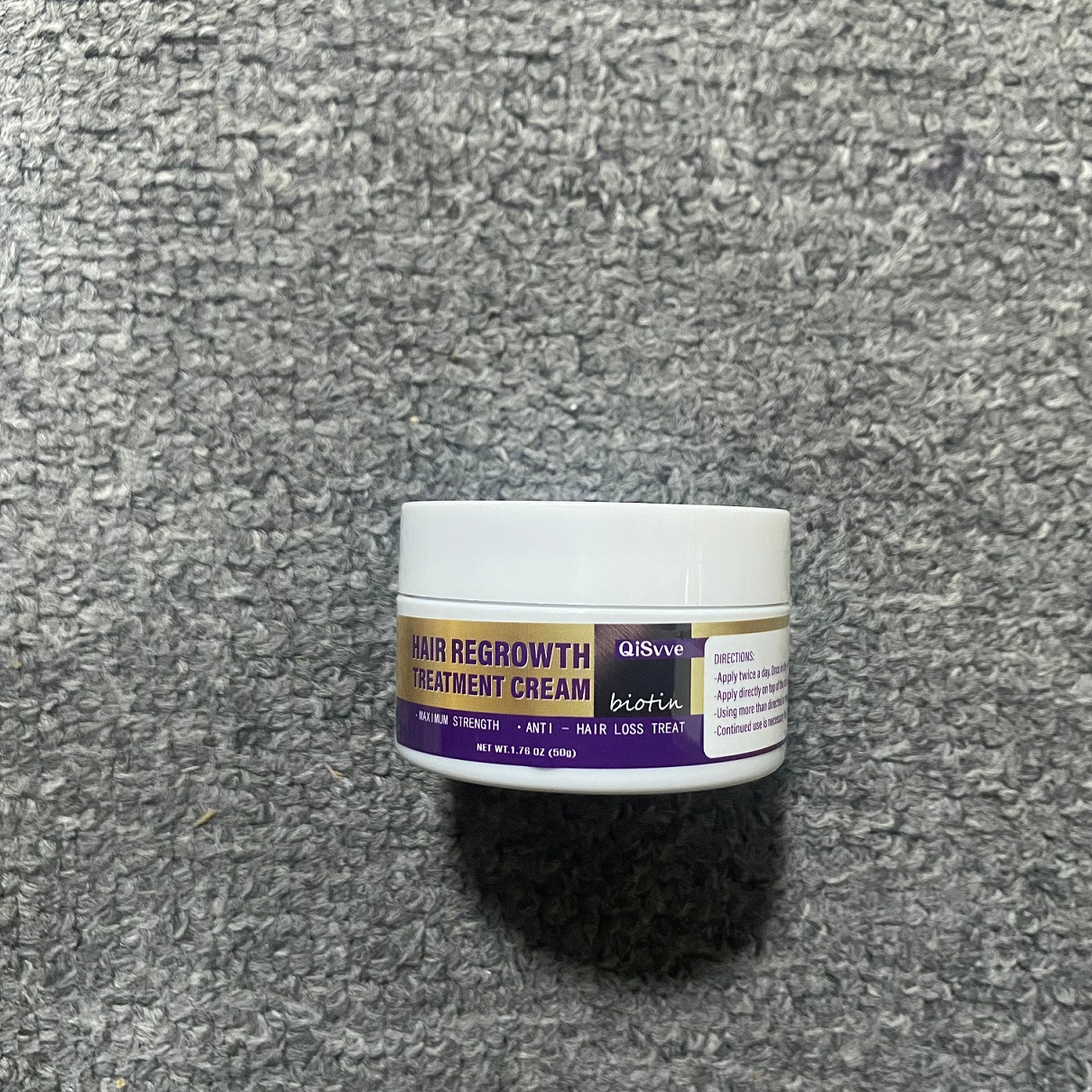 DRUG LABEL: Hair Growth Cream
NDC: 84117-028 | Form: CREAM
Manufacturer: Shenzhen Hengkaifeng Commerce and Trade Co., Ltd
Category: otc | Type: HUMAN OTC DRUG LABEL
Date: 20241011

ACTIVE INGREDIENTS: BIOTIN 0.1 g/100 g
INACTIVE INGREDIENTS: WATER; CAFFEINE

ACTIVE INGREDIENT

Biotin

Purpose

hair care

Use

Hair Cream to help firming hair root and balancing the facial skin secretion, improve the hair itching,remove the grease, clear the hair follicles to promote the hair growth, reduce the hair loss and broken hair, give you a healthy hair looks.

Warnings

For adult external use only. Flammable.
Keep away from heat or flame
Do not use
* Pregnant women and children.
* on open skin wounds

When Using

When using this product keep out of
eyes, ears, and mouth, In case of contact
with eyes,rinse eyes thoroughly with
water. Stop use and ask a doctor if
irritation or rash occurs. These may be
signs of a serious condition.Keep out of
reach of children. If swallowed, get
medical help or contact a Poison Control
Center right away.

Keep Out Of Reach Of Children

Directions Of Safe Use:

* Put right amount of Hair Cream apply on the hair loss area or facial hair, gentle to massage to help absorb.
* 1-2 times per day.

Other information

Store between15-30C(59-86F)
Avoid freezing and excessive heat above
40C (104F)

Inactive ingredients

Batana Oil, Cocos Nucifera Oil, Simmondsia Chinensis Seed Oil, Shea Butter,
Rosmarinus Officinalis Leaf Oil, Tocopheryl, Caffeine, Niacinamide,
Vitamin E, Keratin